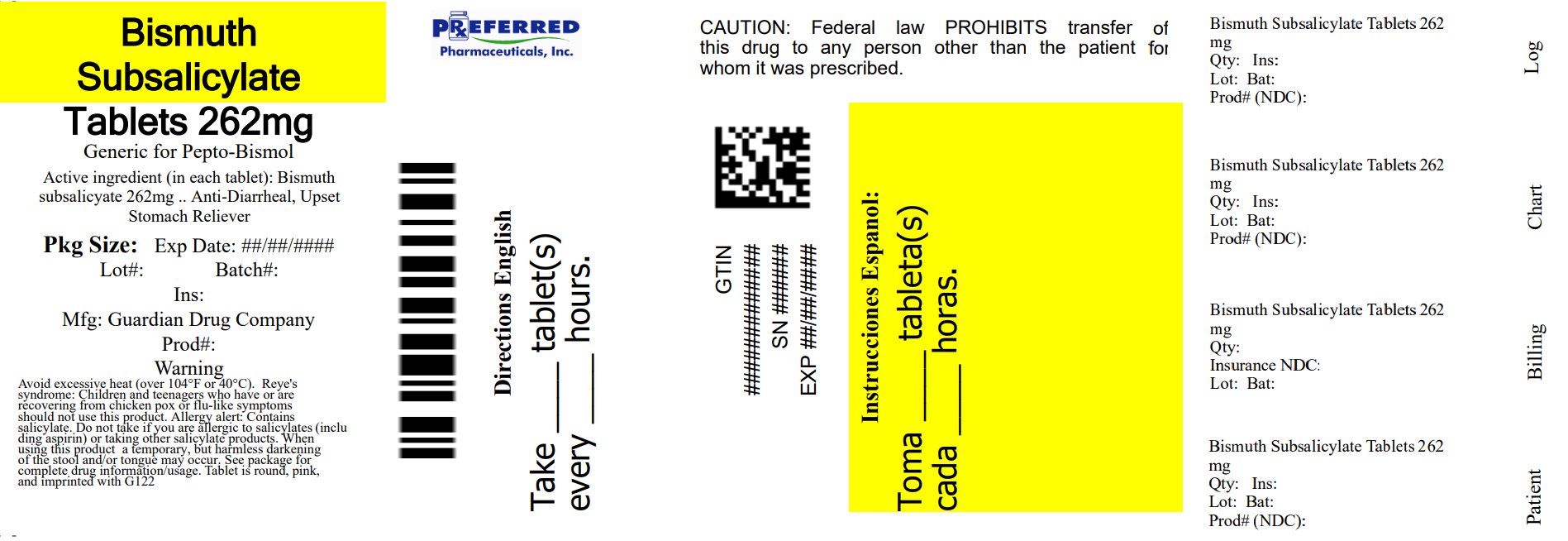 DRUG LABEL: Goodsense Regular strength Stomach Relief 122
NDC: 68788-4002 | Form: TABLET, CHEWABLE
Manufacturer: Preferred Pharmaceuticals Inc.
Category: otc | Type: HUMAN OTC DRUG LABEL
Date: 20250801

ACTIVE INGREDIENTS: BISMUTH SUBSALICYLATE 262 mg/1 1
INACTIVE INGREDIENTS: CALCIUM CARBONATE; D&C RED NO. 27 ALUMINUM LAKE; MAGNESIUM STEARATE; MANNITOL; SACCHARIN SODIUM

Good sense Regular strength stomach relief 122

ACTIVE INGREDIENT(S)

Bismuth subsalicylate 262 mg (total salicylate 102 mg per tablet)

PURPOSE

Upset stomach reliever and anti-diarrheal

USE(S)

relieves:

- diarrhea
- heartburn
- indigestion
- nausea
- upset stomach associated with these symptoms

WARNINGS

Reye's syndrome: Children and teenagers who have or are recovering from chicken pox or flu-like symptoms should not use this product. When using this product, if changes in behavior with nausea and vomiting occur, consult a doctor because these symptoms could be an early sign of Reye’s syndrome, a rare but serious illness.

____________________________________________________________________________________________________________

Allergy alert: Contains salicylate. Do not take if you are

- allergic to salicylates (including aspirin)
- taking other salicylate products

DO NOT USE

if you have

- bloody or black stool
- an ulcer
- a bleeding problem

ASK A DOCTOR BEFORE USE IF YOU HAVE

- fever
- mucus in the stool

ASK A DOCTOR OR PHARMACIST BEFORE USE IF YOU ARE

taking any drug for

- anticoagulation (thinning of the blood)
- diabetes
- gout
- arthritis

WHEN USING THIS PRODUCT

a temporary, but harmless darkening of the stool and/or tongue may occur.

STOP USE AND ASK DOCTOR IF

- symptoms get worse
- ringing in the ears or loss of hearing occurs
- diarrhea lasts more than 2 days

IF PREGNANT OR BREAST-FEEDING,

ask a health professional before use.

KEEP OUT OF REACH OF CHILDREN

In case of overdose, get medical help or contact a Poison Control Center immediately.

DIRECTIONS

- chew or dissolve in mouth
- adults and children 12 years and over: 2 tablets every 1/2 to 1 hour as needed
- do not take more than 8 doses (16 tablets) in 24 hours
- children under 12 years: ask a doctor
- drink plenty of clear fluids to help prevent dehydration caused by diarrhea
- use until diarrhea stops but not more than 2 days

OTHER INFORMATION

- each tablet contains:
- sodium less than 1 mg
- salicylate 102 mg
- very low sodium
- avoid excessive heat (over 104oF or 40oC).
- TAMPER EVIDENT: Do not use if individual compartments are torn or open.

INACTIVE INGRADIENTS

calcium carbonate, D&C red 27 aluminum lake, flavor, Magnesium stearate, mannitol, pregelatinized starch, saccharin sodium.

PRINCIPAL DISPLAY PANEL

OODSENSE ®

Regular Strength

NDC 50804-152-49

Stomach Relief Tablets

Bismuth Subsalicylate 262 mg

Antidiarrheal/Upset Stomach Reliever

Soothing Relief For

5 Symptoms

- Upset Stomach
- Indigestion
- Heartburn
- Nausea
- Diarrhea

Actual Size

* Compare to active ingredient of Pepto-Bismol® Chewable Tablets

30 Chewable Tablets

NDC 68788-4002-3

Relabeled By: Preferred Pharmaceuticals Inc.